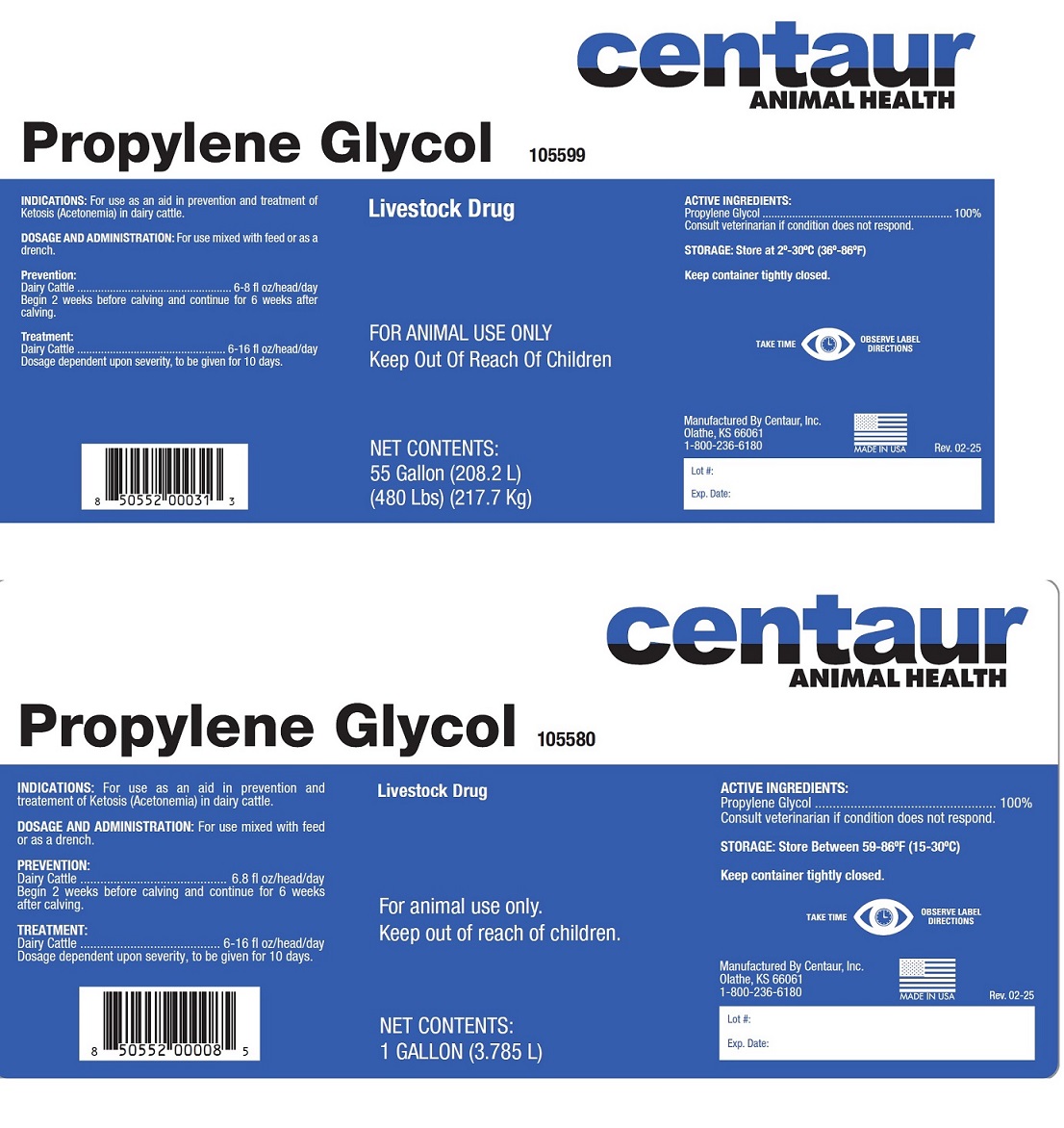 DRUG LABEL: PROPYLENE GLYCOL
NDC: 58305-055 | Form: LIQUID
Manufacturer: Centaur, Inc.
Category: animal | Type: OTC ANIMAL DRUG LABEL
Date: 20250306

ACTIVE INGREDIENTS: PROPYLENE GLYCOL 3.785 L/3.785 L

INDICATIONS AND USAGE

PROPYLENE GLYCOL

For Animal Use Only

Keep Out of Reach of Children

LIVESTOCK DRUG

INDICATIONS

For use as an aid in prevention and treatment for Ketosis (Acetonemia) in dairy cattle.

ACTIVE INGREDIENTS

Propylene Glycol ...................... 100%

Consult veterinarian if condition does not respond.

DOSAGE AND ADMINISTRATION

For use mixed with feed or as a drench.

Prevention:

Dairy Cattle .................6-8 fl oz/head/day
Begin 2 weeks before calving and continue for 6 weeks after calving.

Treatment:

Dairy Cattle .................6-16 fl oz/head/day
Dosage dependent upon severity, to be given for 10 days.

Store at 2o-30oC (36o-86oF)

Keep container tightly closed.